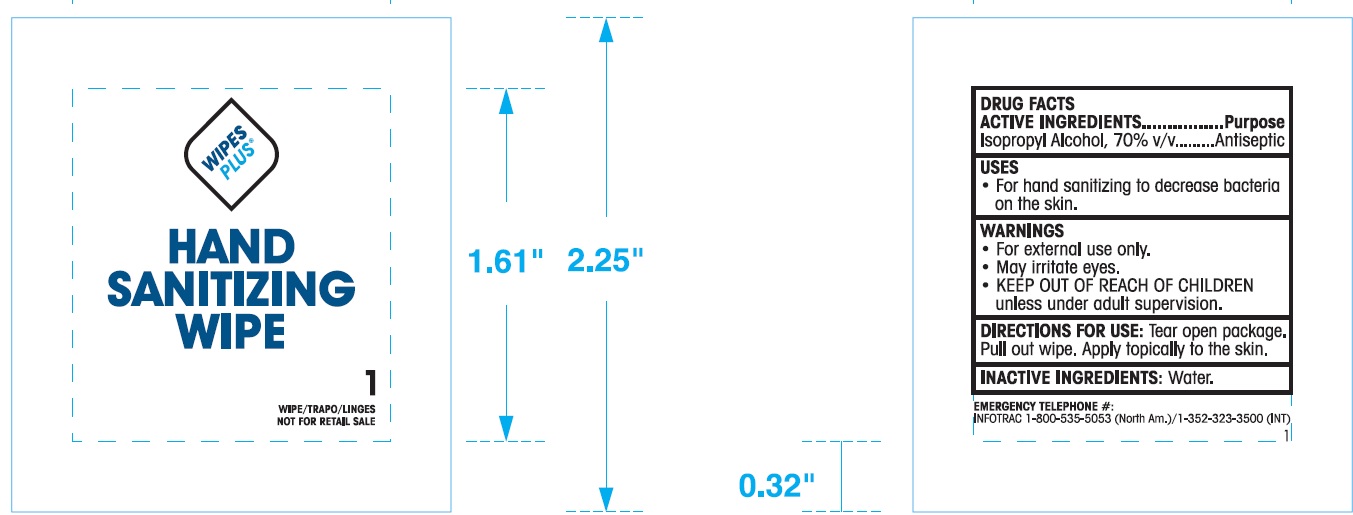 DRUG LABEL: Wipes Plus
NDC: 67151-505 | Form: SWAB
Manufacturer: Progressive Products, LLC
Category: otc | Type: HUMAN OTC DRUG LABEL
Date: 20221014

ACTIVE INGREDIENTS: ISOPROPYL ALCOHOL 70 mL/100 mL
INACTIVE INGREDIENTS: WATER

DRUG FACTS

Active Ingredient

Isopropyl Alcohol 70% v/v

Purpose

Antiseptic

Uses

For hand sanitizing to decrease bacteria on the skin.

Warnings

- For external use only
- May irritate eyes

KEEP OUR OF REACH OF CHILDREN unless under adult supervision

Directions

Tear open package. Pull out wipe. Apply topically to the skin

Inactive Ingredients

Water

Questions or Comments

EMERGENCY TELEPHONE #

INFOTRAC 1-800-535-5053 (North Am.)

1-352-323-3500 (INT.)

Principal Display Panel

NDC 67151-505-02

WIPES PLUS®

HAND SANITIZING WIPE

1 WIPE/TRAPO/LINGES

NOT FOR RETAIL SALE

REORDER NO/ITEM NO 35014